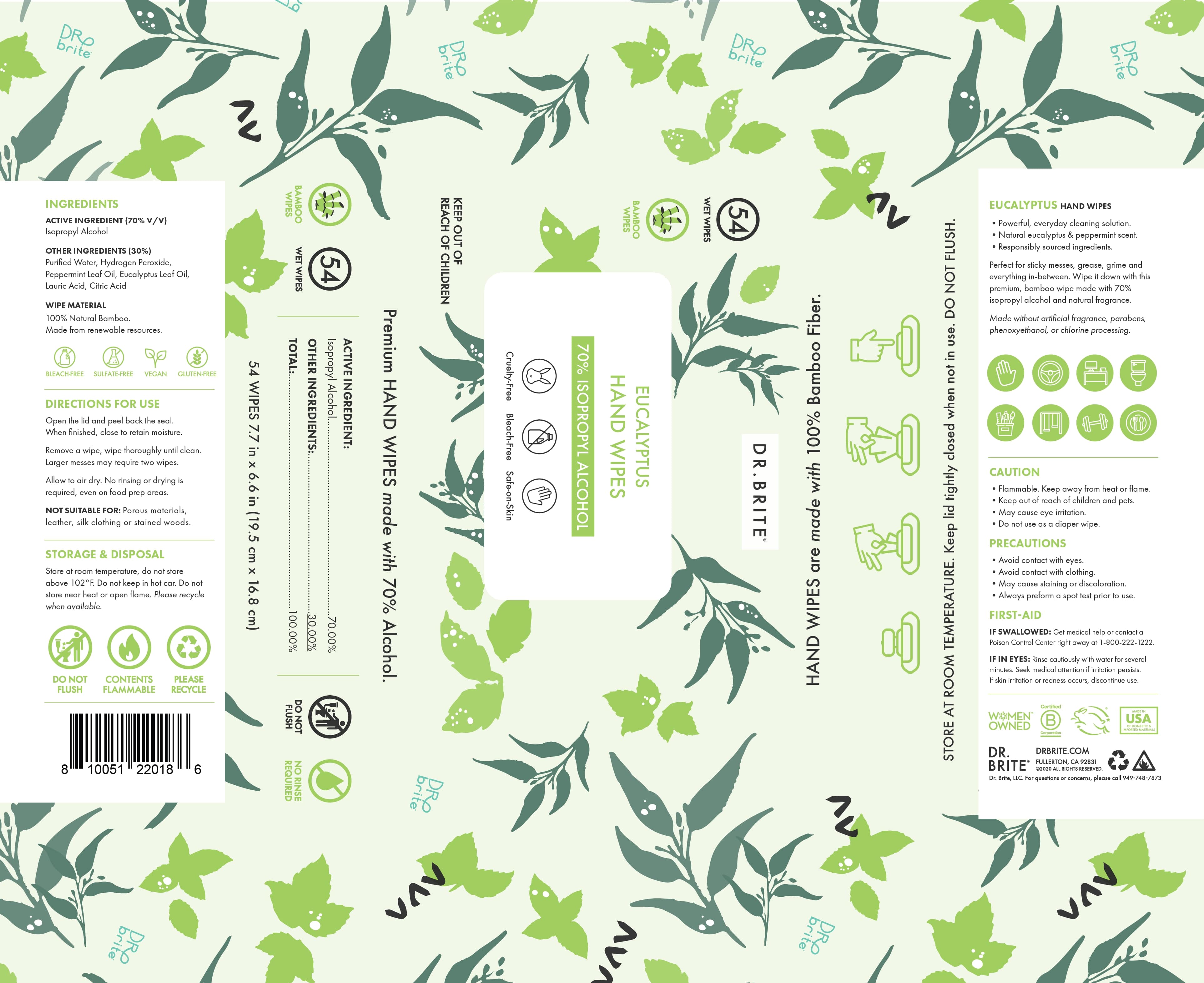 DRUG LABEL: Eucalyptus Hand Wipes
NDC: 74110-002 | Form: CLOTH
Manufacturer: Dr. Brite
Category: otc | Type: HUMAN OTC DRUG LABEL
Date: 20220216

ACTIVE INGREDIENTS: ISOPROPYL ALCOHOL 70 mL/100 mL
INACTIVE INGREDIENTS: EUCALYPTUS PIPERITA LEAF OIL; CITRIC ACID MONOHYDRATE; HYDROGEN PEROXIDE; WATER; PEPPERMINT OIL; LAURIC ACID

Dr. Brite Eucalyptus Hand Wipes

Active Ingredient(s)

Isopropyl Alcohol 70% v/v.

PURPOSE

Antiseptic

Inactive ingredients

Purifies Water, Hydrogen Peroxide, Peppermint Leaf Oil, Eucalyptus Leaf Oil, Lauric Acid, Citric Acid.

DOSAGE AND ADMINISTRATION

Directions For Use

Open the lid and peel back the seal. When finished, close to retain moisture.

Remove a wipe, wipe thoroughly until clean. Larger messes may require two wipes.

Allow to air dry. No rinsing or drying is required, even on food prep areas.

NOT SUITABLE FOR: Porous materials, leather, silk clothing or stained woods.

Storage & Disposal

Store at room temperature, do not store above 102°F. DO not keep in hot car. Do not store near heat or open flame. Please recycle when available.

Caution

- Flammable. Keep away from heat or flame.
- Keep out of reach of children and pets.
- May cause eye irritation.
- Do not use as a diaper wipe.

Precautions

- Avoid contact with eyes.
- Avoid contact with clothing.
- May cause staining or discoloration.
- Always perform a spot test prior to use.

Keep out of reach of children and pets.

First-Aid

IF SWALLOWED: Get medical help or contact a Poison Control Center right away at 1-800-222-1222.

IF IN EYES: Rinse cautiously with water for several minutes. Seek medical attention if irritation persists. If skin irritation or redness occurs, discontinue use.

For questions or concerns, please call 949-748-7873